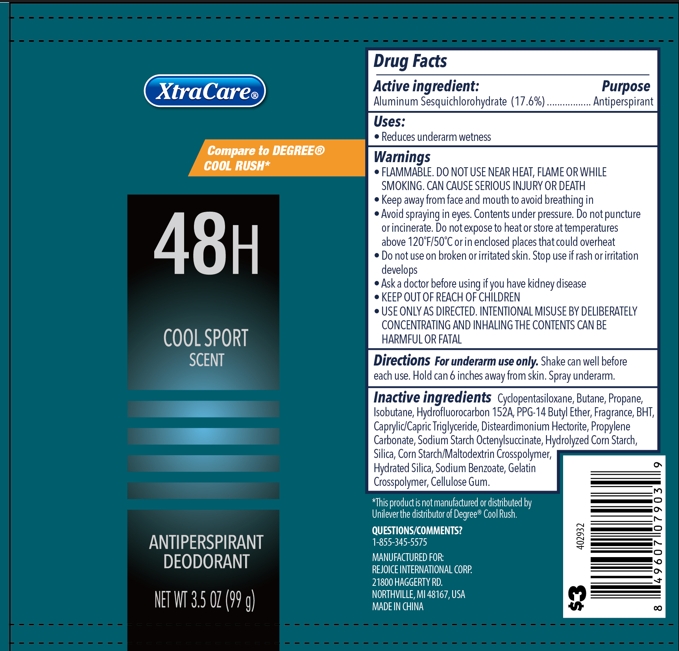 DRUG LABEL: Dry Cool Sport 3.5oz
NDC: 57337-176 | Form: SPRAY
Manufacturer: Rejoice International Corp.
Category: otc | Type: HUMAN OTC DRUG LABEL
Date: 20250125

ACTIVE INGREDIENTS: ALUMINUM SESQUICHLOROHYDRATE 17.6 g/100 g
INACTIVE INGREDIENTS: CELLULOSE GUM; HYDRATED SILICA; SODIUM BENZOATE; GELATIN, UNSPECIFIED; HYDROFLUOROCARBON 152A; ISOBUTANE; BUTANE; STARCH, CORN; PROPANE; DISTEARDIMONIUM HECTORITE; PROPYLENE CARBONATE; CYCLOPENTASILOXANE; PPG-14 BUTYL ETHER; CAPRYLIC/CAPRIC TRIGLYCERIDE; BHT; CORN SYRUP; SILICA; ALUMINUM STARCH OCTENYLSUCCINATE

Dry Spray Cool Sport 3.5oz

Active ingredient

Aluminum Sesquichlorohydrate 17.6%

Purpose

Antiperspirant

Use

Reduces underarm wetness

Warnings

FLAMMABLE. DO NOT USE NEAR HEAT, FLAME OR WHILE SMOKING. CAN CAUSE SERIOUS INJURY OR DEATH.

- USE ONLY AS DIRECTED. INTENTIONAL MISUSE BY DELIBERATELY CONCENTRATING AND INHANDLING THE CONTENTS CAN BE HARMFUL OR FATAL.

When using

- Keep away from face and mouth to avoid breathing in
- Avoid spraying in eyes. Contents under pressure. Do not punture or incinerate. Do not expose to heat or store at temperatures above 120 F/50 C or in enclosed places that could overheat

Do not use on broken or irritated skin.

Stop use

Stop use if rash or irritation develops

Ask a doctor before using if you have kidney disease

KEEP OUT OF REACH OF CHILDREN

Directions

For underarm use only. Shake can well before each use. Hold can 6 inches away from skin. Spray underarm.

Inactive ingredients

Cyclopentasiloxane

Butane

Propane

Isobutane

Hydrofluorocarbon 152A

PPG-14 Butyl Ether

Fragrance

BHT

Caprylic/Capric Triglyceride

Disteardimonium Hectorite

Propylene Carbonate

Sodium Starch Octenylsuccinate

Hydrolyzed Corn Starch

Silica

Corn Starch/Maltodextrin Crosspolymer

Hydrated Silica

Sodium Benzoate

Gelatin Crosspolymer

Cellulose Gum